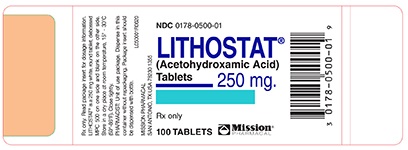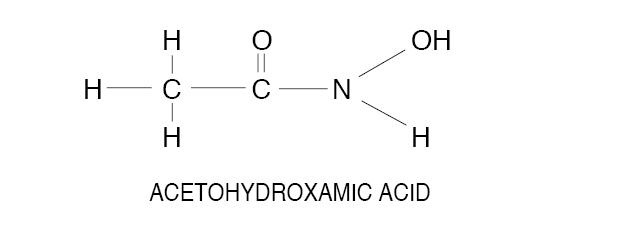 DRUG LABEL: Lithostat
NDC: 0178-0500 | Form: TABLET
Manufacturer: Mission Pharmacal Company
Category: prescription | Type: HUMAN PRESCRIPTION DRUG LABEL
Date: 20240108

ACTIVE INGREDIENTS: ACETOHYDROXAMIC ACID 250 mg/1 1
INACTIVE INGREDIENTS: CELLULOSE, MICROCRYSTALLINE 240 mg/1 1; SILICON DIOXIDE 5 mg/1 1; MAGNESIUM STEARATE 3 mg/1 1; PEPPERMINT OIL 0.2 mg/1 1

LITHOSTAT®
(Acetohydroxamic Acid) Tablets

DESCRIPTION

Acetohydroxamic acid (AHA) is a stable, synthetic compound derived from hydroxylamine and ethyl acetate. Its molecular structure is similar to urea:

AHA is weakly acidic, highly soluble in water, and chelates metals - notably iron. The molecular weight is 75.068. AHA has a pKa of 9.32 and a melting point of 89-91° C. AHA is a urease inhibitor. Available as 250 mg tablets.

CLINICAL PHARMACOLOGY

AHA reversibly inhibits the bacterial enzyme urease, thereby inhibiting the hydrolysis of urea and production of ammonia in urine infected with urea-splitting organisms. The reduced ammonia levels and decreased pH enhance the effectiveness of antimicrobial agents and allow an increased cure rate of these infections.

AHA is well absorbed from the gastrointestinal tract after oral administration; peak blood levels occur from 0.25 to 1 hour after dosing. The compound is distributed throughout body water, and there is no known binding to any tissue. AHA chelates with dietary iron within the gut. This reaction may interfere with absorption of AHA and with iron. Concomitant hypochromic anemia should be treated with intramuscular iron.

In rodents, the metabolic fate of AHA is well known; 55% is excreted unchanged in urine, 25% is excreted as acetamide or acetate and 7% is excreted by the lungs as carbon dioxide. Less than 1% is excreted in the feces. Approximately 5% of the administered dose is unaccounted for. In rodents, AHA shows a dose-related change in pharmacokinetics; with increasing dose, there is an increase in the half-life and an increase in the percent of the administered dose recovered in urine as unchanged AHA.

Pharmacokinetics in man are generally similar to rodents including the dose-related increase in half-life, but they are not as well characterized as in the rodent. Thirty-six to sixty-five percent (36-65%) of the oral dosage is excreted unchanged in the urine. It is unaltered AHA in the urine that provides the therapeutic effect, but the precise concentration of AHA in urine that is necessary to inhibit urease is incompletely delineated. Therapeutic benefit may be obtained from concentrations as low as 8 mcg/ml; higher concentrations (i.e., 30 mcg/ml) are expected to provide more complete inhibition of urease. The plasma half-life of AHA is approximately 5-10 hours in subjects with normal renal function and is prolonged in patients with reduced renal function.

Acetohydroxamic acid has been evaluated clinically in patients with urea-splitting urinary infections, often accompanied by struvite stone disease, that were recalcitrant to other forms of medical and surgical management. In these clinical trials, AHA reduced the pathologically elevated urinary ammonia and pH levels that result from the hydrolysis of urea by the enzyme, urease.

AHA does not acidify urine directly nor does it have a direct antibacterial effect. The usefulness of reducing ammonia levels and decreasing urinary pH is suggested by single (not yet replicated) clinical trials in which urease inhibition 1) allowed successful antibiotic treatment of urea-splitting Proteus infections after surgical removal of struvite stones in patients not cured by 3 months of antibacterial treatment alone, and 2) reduced the rate of stone growth in patients who were not candidates for surgical removal of stones.

INDICATIONS AND USAGE

Acetohydroxamic acid is indicated as adjunctive therapy in patients with chronic urea-splitting urinary infection. AHA is intended to decrease urinary ammonia and alkalinity, but it should not be used in lieu of curative surgical treatment (for patients with stones) or antimicrobial treatment. Long-term treatment with AHA may be warranted to maintain urease inhibition as long as urea-splitting infection is present. Experience with AHA does not go beyond 7 years. A patient package insert should be distributed to each patient who receives AHA.

CONTRAINDICATIONS

Acetohydroxamic acid
should not be used in:
a. patients whose physical state and disease are amenable to definitive surgery and appropriate antimicrobial agents
b. patients whose urine is infected by non-urease producing organisms
c. patients whose urinary infections can be controlled by culture-specific oral antimicrobial agents
d. patients whose renal function is poor (i.e., serum creatinine more than 2.5 mg/dl and/or creatinine clearance less than 20 ml/min)
e. female patients who do not evidence a satisfactory method of contraception
f. patients who are pregnant

Acetohydroxamic acid may cause fetal harm when administered to a pregnant woman. AHA was teratogenic (retarded and/or clubbed rear leg at 750 mg/kg and above and exencephaly and encephalocele at 1,500 mg/kg) when given intraperitoneally to rats.
AHA is contraindicated in women who are or may become pregnant. If this drug is used during pregnancy, or if the patient becomes pregnant while taking this drug, the patient should be informed of the potential hazard to the fetus.

WARNINGS

A Coombs negative hemolytic anemia has occurred in patients receiving AHA. Gastrointestinal upset characterized by nausea, vomiting, anorexia and generalized malaise have accompanied the most severe forms of hemolytic anemia. Approximately 15% of patients receiving AHA have had only laboratory findings of an anemia. However, most patients developed a mild reticulocytosis. The untoward reactions have reverted to normal following cessation of treatment. A complete blood count, including a reticulocyte count, is recommended after two weeks of treatment. If the reticulocyte count exceeds 6%, a reduced dosage should be entertained. A CBC and reticulocyte count are recommended at 3-month intervals for the duration of treatment.

PRECAUTIONS

General

Hematologic Effects: Bone marrow depression (leukopenia, anemia, and thrombocytopenia) has occurred in experimental animals receiving large doses of AHA, but has not been seen in man to date. AHA is a known inhibitor of DNA synthesis and also chelates metals - notably iron. Its bone marrow suppressant effect is probably related to its ability to inhibit DNA synthesis, but anemia could also be related to depletion of iron stores. To date, the only clinical effect noted has been hemolysis, with a decrease in the circulating red blood cells, hemoglobin and hematocrit. Abnormalities in platelet or white blood cell count have not been noted. However, clinical monitoring of the platelet and white cell count is recommended.

Monitoring Liver Function: Abnormalities of liver function have not been reported to date. However, a chloro-benzene derivative of acetohydroxamic acid caused significant liver dysfunction in an unrelated study. Therefore, close monitoring of liver function is recommended. (See Carcinogenesis for discussion of possible hepatic carcinogenesis.)

Use In Patients With Renal Impairment: Since AHA is eliminated primarily by the kidneys, patients with significantly impaired renal function should be closely monitored, and a reduction of daily dose may be needed to avoid excessive drug accumulation. (See Dosage and Administration.)

DRUG INTERACTIONS

AHA has been used concomitantly with insulin, oral and parenteral antibiotics, and progestational agents. No clinically significant interactions have been noted, but until wider clinical experience is obtained, AHA should be used with caution in patients receiving other therapeutic agents.

AHA taken in association with alcoholic beverages has resulted in a rash. (See Adverse Reactions.)

AHA chelates heavy metals-notably iron. The absorption of iron and AHA from the intestinal lumen may be reduced when both drugs are taken concomitantly. When iron administration is indicated, intramuscular iron is probably the product of choice.

CARCINOGENESIS, MUTAGENESIS, IMPAIRMENT OF FERTILITY

Well controlled, long-term animal studies that identify the carcinogenic potential of AHA treatment have not been conducted. Acetamide, a metabolite of AHA, has been shown to cause hepatocellular carcinoma in rats at oral doses 1,500 times the human dose. AHA is cytotoxic and was positive for mutagenicity in the Ames test.

PREGNANCY

(See Contraindications.)

NURSING MOTHERS

It is not known whether AHA is secreted in human milk. Because many drugs are excreted in human milk, and because of the potential for serious adverse reactions in nursing infants from AHA, a decision should be made to discontinue nursing or the drug, taking into account the significance of the drug to the mother’s well being.

PEDIATRIC USE

Children with chronic, recalcitrant, urea-splitting urinary infection may benefit from treatment with AHA. However, detailed studies involving dosage and dose intervals in children have not been established. Children have tolerated a dose of 10 mg/kg/day, taken in two or three divided doses, satisfactorily for periods up to one year. Close monitoring of such patients is mandatory.

ADVERSE REACTIONS

Experience with AHA is limited. About 150 patients have been treated, most for periods of more than a year.

Adverse reactions have occurred in up to thirty percent (30%) of the patients receiving AHA. In some instances the reactions were symptomatic; in others only changes in laboratory parameters were noted. Adverse reactions seem to be more prevalent in patients with preexisting thrombophlebitis or phlebothrombosis and/or in patients with advanced degrees of renal insufficiency. The risk of adverse reactions is highest during the first year of treatment. Chronic treatment does not seem to increase the risk nor the severity of adverse reactions.

The following reactions have been reported:

NEUROLOGICAL: Mild headaches are commonly reported (about 30%) during the first 48 hours of treatment. These headaches are mild, responsive to oral salicylate-type analgesics, and usually disappear spontaneously. The headaches have not been associated with vertigo, tinnitus, or visual or auditory abnormalities. Tremulousness and nervousness have also been reported.

GASTROINTESTINAL: Gastrointestinal symptoms, nausea, vomiting, anorexia, and malaise have occurred in 20-25% of patients. In most patients the symptoms were mild, transitory, and did not result in interruption of treatment. Approximately 3% of patients developed a hemolytic anemia of sufficient magnitude to warrant interruption in treatment; several of these patients also had symptoms of gastrointestinal upset.

HEMATOLOGICAL: Approximately 15% of patients have had laboratory findings characteristic of a hemolytic anemia. A mild reticulocytosis (5- 6%) without anemia, is even more prevalent. The laboratory findings are occasionally accompanied by systemic symptoms such as malaise, lethargy and fatigue, and gastrointestinal symptoms. Symptoms and laboratory findings have invariably improved following cessation of treatment with AHA. The hematological abnormalities are more prevalent in patients with advanced renal failure.

DERMATOLOGICAL: A nonpruritic, macular skin rash has occurred in the upper extremities and on the face of several patients taking AHA on a long-term basis, usually when AHA has been taken concomitantly with alcoholic beverages, but in a few patients in the absence of alcohol consumption. The rash commonly appears 30-45 minutes after ingestion of alcoholic beverages; it characteristically disappears spontaneously in 30-60 minutes. The rash may be associated with a general sensation of warmth. In some patients the rash is sufficiently severe to warrant discontinuation of treatment, but most patients have continued treatment, avoiding alcohol or using smaller quantities of it. Alopecia has also been reported in patients taking AHA.

CARDIOVASCULAR: Superficial phlebitis involving the lower extremities has occurred in several patients on AHA during the early (Phase II) clinical trials. Several of the affected patients had had phlebitic episodes prior to treatment. One patient developed deep vein thrombosis of the lower extremities. The patient with phlebothrombosis had an associated traumatic injury to the groin. It is unclear whether the phlebitis was related to or exacerbated by treatment with AHA. No patient in the three (3) year controlled (Phase III) clinical trial developed phlebitis. In all instances these vascular abnormalities returned to normal following appropriate medical therapy. Embolic phenomena have been reported in three patients taking AHA in the Phase II trial. The phlebitis and emboli resolved following discontinuation of AHA and implementation of appropriate medical therapy. Several patients have resumed treatment with AHA without ill effect. Palpitations have also been reported in patients taking AHA.

RESPIRATORY: No symptoms have been reported. Radiographic evidence of small pulmonary emboli has been seen in three patients with phlebitis in their lower legs.

PSYCHIATRIC: Depression, anxiety, nervousness, and tremulousness have been observed in approximately 20% of patients taking AHA. In most patients the symptoms were mild and transitory, but in about 6% of patients the symptoms were sufficiently distressing to warrant interruption or discontinuation of treatment.

OVERDOSAGE

Acute deliberate overdosage in man has not occurred, but would be expected to induce the following symptoms: anorexia, malaise, lethargy, diminished sense of well being, tremulousness, anxiety, nausea and vomiting. Laboratory findings are likely to include an elevated reticulocyte count and a severe hemolytic reaction requiring hospitalization, symptomatic treatment, and possibly blood transfusions. Concomitant reduction in platelets and/or white blood cells should be anticipated.

Milder overdosages resulting in hemolysis have occurred in an occasional patient with reduced renal function after several weeks or months of continuous treatment.

The acute LD 50 of AHA in animals (rats) is 4.8 gm/kg.

Recommended treatment for an overdosage reaction consists of (1) cessation of treatment, (2) close monitoring of hematologic status, (3) symptomatic treatment, and (4) blood transfusions as required by the clinical circumstances. The drug is probably dialyzable, but this property has not been tested clinically.

DOSAGE AND ADMINISTRATION

AHA should be administered orally, one tablet 3-4 times a day in a total daily dose of 10-15 mg/kg/day. The recommended starting dose is 12 mg/kg/day, administered at 6-8 hour intervals at a time when the stomach is empty. The maximum daily dose should be no more than 1.5 grams, regardless of body weight.

The dosage should be reduced in patients with reduced renal function. Patients whose serum creatinine is greater than 1.8 mg/dl should take no more than 1.0 gm/day; such patients should be dosed at q-12-h intervals. Further reductions in dosage to prevent the accumulation of toxic concentrations in the blood may also be desirable. Insufficient data exists to accurately characterize the optimum dose and/or dose interval in patients with moderate degrees of renal insufficiency.

Patients with advanced renal insufficiency (i.e., serum creatinine more than 2.5 mg/dl) should not be treated with AHA. The risk of accumulation of toxic blood levels of AHA seems to be greater than the chances for a beneficial effect in such patients.

In children an initial dose of 10 mg/kg/day is recommended. Close monitoring of the patient’s clinical condition and hematologic status is recommended. Titration of the dose to higher or lower levels may be required to obtain an optimum therapeutic effect and/or to reduce the risk of side effects.

HOW SUPPLIED

LITHOSTAT®, NDC 0178-0500-01, is available for oral administration as 250 mg white, round tablets, in unit of use packages of 100 tablets. Each LITHOSTAT®tablet is debossed MPC 500 on one side and blank on the other side. LITHOSTAT®should be stored in a dry place at room temperature, 15° - 30°C (59° - 86°F). Container should be closed tightly.

L050001R0620

PATIENT INFORMATION

PLEASE READ THIS INFORMATION BEFORE USING THIS DRUG.

GENERAL INFORMATION:It has been known for many years that urinary infection may cause the formation of urinary stones. As these stones form, bacteria are trapped within the stones. The trapped bacteria cause the stones to grow, and the stones protect the bacteria from antibiotics. Surgical removal of the stone attempts to break this vicious cycle - many times successfully. However, if infection persists or if a small stone fragment persists, then there is an increased risk of stone recurrence. Multiple operations to remove kidney stones may result in damage and scarring of the kidney. In some situations removal of the kidney may be necessary.

In some instances stones may form initially as a result of non-infectious (i.e., metabolic) causes. If a metabolic stone becomes infected, then an “infection stone” may grow onto the “metabolic stone.” Stone analysis and/or biochemical tests will usually determine which factors are present.

Experimental investigations have identified an enzyme called urease which is made by some (but not all) bacteria. Urease reacts with urine to make ammonia. Ammonia changes the acidity of the urine and the change in acidity encourages stone formation. LITHOSTAT®(acetohydroxamic acid) inhibits urease and thereby reduces urinary ammonia. In some instances, LITHOSTAT®enhances the effectiveness of antibiotics and thereby makes urinary infection easier to control.
WHAT IS LITHOSTAT®? LITHOSTAT®is a drug which prevents the excessive buildup of ammonia in your urine, which controls the acidity and alkalinity (pH) of your urine. The cause of excessive ammonia and alkalinity in your urine is a bacterial infection.

WHAT CAN LITHOSTAT®DO? Treatment with LITHOSTAT®is prescribed to decrease urinary ammonia. This may increase the chance of controlling your infection with antibiotics and may help the treatment of your kidney stones. Dissolution of existing stones is unlikely.

LITHOSTAT®should not be used in place of surgical treatment. Surgical removal of all stones and elimination of all infection with antibiotics offers the possibility of curative treatment. LITHOSTAT®is likely to be more effective after large stones or obstructing stones have been removed.

WHAT ARE THE PROBLEMS OR SIDE EFFECTS WITH LITHOSTAT®? The complete spectrum of side effects induced by LITHOSTAT®(acetohydroxamic acid) is unknown. However, some side effects which have been reported to date have been headaches, abdominal discomfort, nausea, loss of hair, shakiness, and anemia. Lifethreatening problems (blood clot in the legs) occurred in several patients with advanced disease in early investigation. In more extensive later investigations, this problem has not occurred. No patient has died as a consequence of taking LITHOSTAT®. The most serious side effects seem to occur in patients with poor kidney function and/or in patients with a previous history of these conditions.

Problems related to LITHOSTAT®have disappeared following cessation of the drug and initiation of appropriate medical treatment. Most patients have resumed treatment without ill effect.

A flushing skin reaction (i.e., redness, warmth, and tingling) has occurred in several patients who consumed alcohol during treatment with LITHOSTAT®. The reaction persisted approximately 30 minutes and disappeared without treatment. The cause and significance of this reaction are unknown. Consequently, patients are encouraged to abstain from consumption of alcoholic beverages while being treated with LITHOSTAT®.

In animal studies doses of LITHOSTAT®about 20 times the maximum human dose have caused fetal abnormalities (birth defects) indicating a potential for such an adverse effect in an exposed human fetus. Therefore, LITHOSTAT®should not be given to pregnant women or to any sexually active woman of child-baring age, not using a highly effective method of contraception (oral contraceptive or IUD).

An acceptable long-term study of the cancer causing potential of LITHOSTAT®has not been conducted, but a known metabolite of LITHOSTAT®, acetamide, is carcinogenic (cancer-causing) to the liver in rats at doses about 80 times the maximum human dose of LITHOSTAT®. LITHOSTAT®thus must be considered a potential human carcinogen. LITHOSTAT®kills tissue cells grown in tissue culture and alters genetic material in cells grown in culture.

LITHOSTAT®may induce other adverse reactions which have not yet been recognized.

Unusual symptoms should be reported to your physician. Mild symptoms usually do not warrant discontinuation of treatment. Severe symptoms may necessitate temporary cessation of treatment and/or alteration of dosage.

WHAT ABOUT TAKING OTHER DRUGS WITH LITHOSTAT®? Only take those drugs prescribed by your physician. Do not take prescription drugs or over the counter preparations without your physician‘s specific prescription or recommendation. Drugs that contain iron should not be taken at the same time as LITHOSTAT®, (acetohydroxamic acid).

LITHOSTAT®reacts with iron, and may not be absorbed into the bloodstream. Both the iron you take and the LITHOSTAT®you take may be ineffective if both drugs are taken together.

HOW IMPORTANT IS MY DAILY DOSAGE OF LITHOSTAT®?If you fail to follow your daily dosage schedule with LITHOSTAT®you will probably suffer a setback in treatment effectiveness and new kidney stone formation is likely. LITHOSTAT®plus antibiotic therapy must be taken exactly as your physician prescribes it for optimum effectiveness.

IN CONCLUSION:Your daily dosage of LITHOSTAT®(acetohydroxamic acid) is important to the proper treatment of your condition. Any unusual side effects should be reported to your physician at once.

C08 Rev 010060

MISSION PHARMACAL COMPANY, San Antonio, TX 78230 1355

Lithostat 250mg Label
NDC: 0178-0500-01